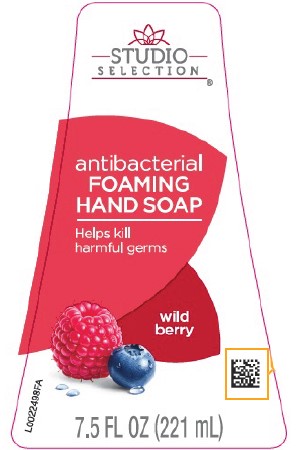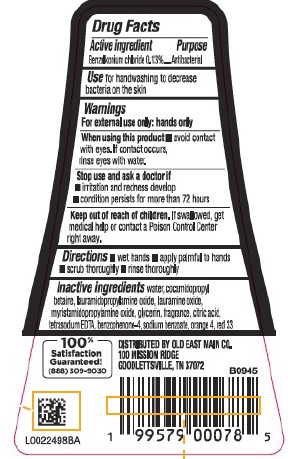 DRUG LABEL: Benzalkonium chloride
NDC: 75712-416 | Form: LIQUID
Manufacturer: Old East Main Co.
Category: otc | Type: HUMAN OTC DRUG LABEL
Date: 20260302

ACTIVE INGREDIENTS: BENZALKONIUM CHLORIDE 1.3 mg/1 mL
INACTIVE INGREDIENTS: SULISOBENZONE; D&C ORANGE NO. 4; GLYCERIN; MYRISTAMIDOPROPYLAMINE OXIDE; LAURAMIDOPROPYLAMINE OXIDE; CITRIC ACID; SODIUM BENZOATE; LAURAMINE OXIDE; COCAMIDOPROPYL BETAINE; D&C RED NO. 33; WATER; EDETATE SODIUM

Studio Selection 416.002/416AC
Energy Berry Antibacterial Foaming Hand Soap

Active ingredient

Benzalkonium chloride 0.13%

Purpose

Antibacterial

Use

for handwashing to decrease bacteria on the skin

Warnings

For external use only: hands only

When using this product

- avoid contact with eyes. If contact occurs, rinse eyes with water.

Stop use and ask a doctor if

- irritation and redness develop
- condition persists for more than 72 hours

Keep out of reach of children.

If swallowed, get medical help or contact a Poison Control Center right away.

Directions

- wet hands
- apply palmful to hands
- scrub thoroughly
- rinse thoroughly

Inactive Ingredients

water, cocamidopropyl betaine, lauramidopropylamine oxide, lauramine oxide, myristamidopropylamine oxide, glycerin, fragrance, citric acid, tetrasodium EDTA, benzophenone-4, sodium benzoate, orange 4, red 33

Adverse Reaction

100% Satisfaction Guaranteed! (888) 309-9030

DISTRIBUTED BY OLD EAST MAIN CO.

100 MISSION RIDGE

GOODLETTSVILLE, TN 37072

Principal Display Panel

STUDIO SELECTION®

antibacterial

FOAMING HAND SOAP

Helps kill harmful germs

wild berry

7.5 FL OZ (221 mL)